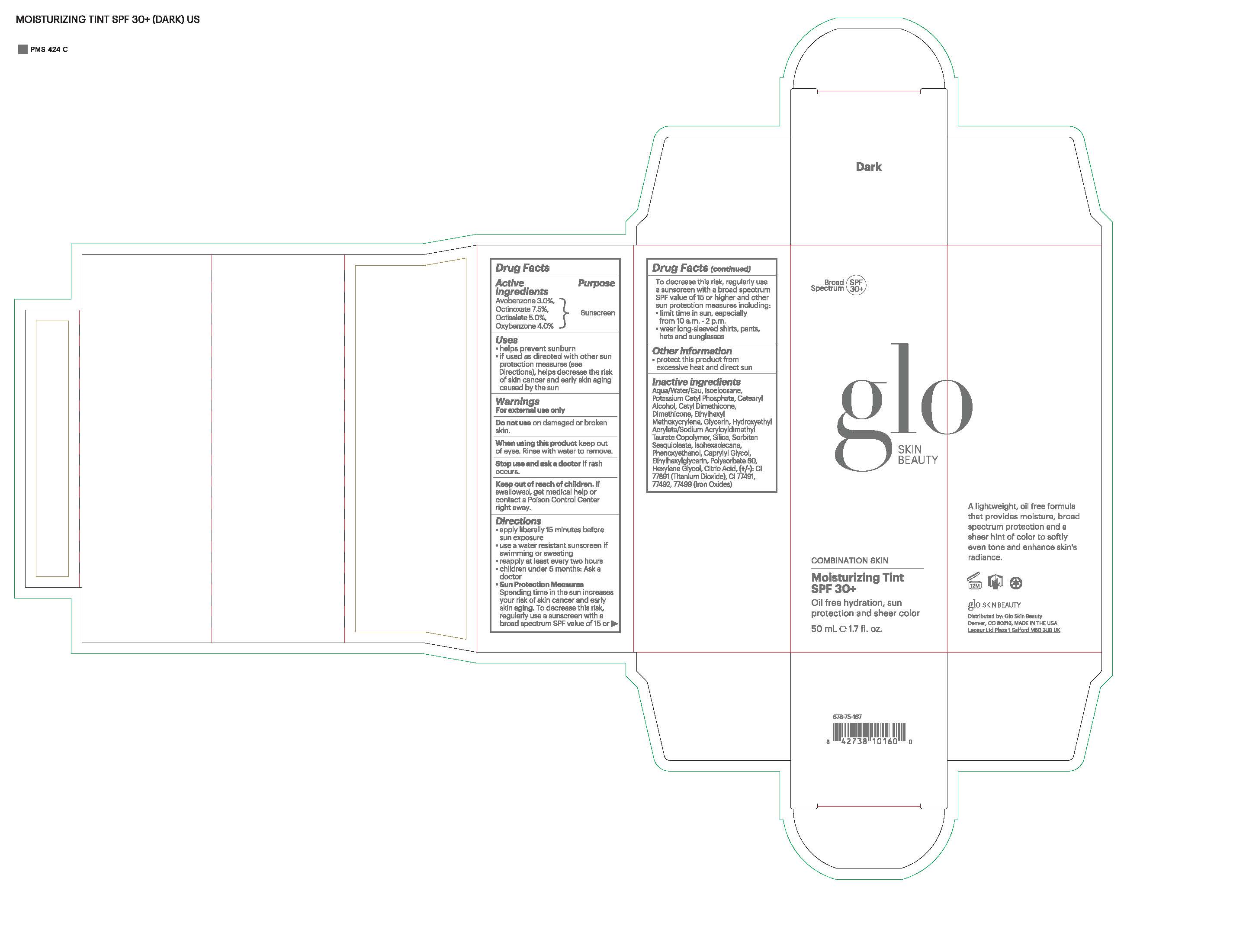 DRUG LABEL: glo SKIN BEAUTY Moisturizing Tint SPF 30
NDC: 60541-1110 | Form: LOTION
Manufacturer: Hayden Caleel LLC
Category: otc | Type: HUMAN OTC DRUG LABEL
Date: 20250109

ACTIVE INGREDIENTS: AVOBENZONE 3 g/100 g; OCTINOXATE 7.5 g/100 g; OCTISALATE 5 g/100 g; OXYBENZONE 4 g/100 g
INACTIVE INGREDIENTS: WATER; POTASSIUM CETYL PHOSPHATE; DIMETHICONE; CETYL DIMETHICONE 25; ETHYLHEXYL METHOXYCRYLENE; GLYCERIN; HYDROXYETHYL ACRYLATE/SODIUM ACRYLOYLDIMETHYL TAURATE COPOLYMER (100000 MPA.S AT 1.5%); SILICON; SORBITAN SESQUIOLEATE; ISOHEXADECANE; PHENOXYETHANOL; CAPRYLYL GLYCOL; ETHYLHEXYLGLYCERIN; POLYSORBATE 60; HEXYLENE GLYCOL; CITRIC ACID ACETATE

DRUG FACTS

Active Ingredients

Avobenzone 3.0%

Octinoxate 7.5%

Octisalate 5.0%

Oxybenzone 4.0%

Uses

• helps prevent sunburn • if used as directed with other
sun protection measures (see Directions), decreases the
risk of skin cancer and early skin aging caused by the sun

Warnings

For external use only
Do not use on damaged or broken skin
When using this product keep out of eyes. Rinse with water to remove.
Stop use and ask a docor if rash occurs
Keep out of reach of children. If swalled, get medical help or contact a Poison Control Center right away.

Directions

• apply generously 15 minutes before sun exposure
• reapply at least every 2 hours
• use a water-resistant sunscreen if swimming or sweating
• Sun Protection Measures. Spending time in the sun
increases your risk of skin cancer and early skin aging. To decrease
this risk, regularly use a sunscreen with a Broad Spectrum SPF
value of 15 or higher and other sun protection measures including:
• limit time in the sun, especially from 10 a.m. - 2 p.m.
• wear long-sleeved shirts, pants, hats, and sunglasses
• children under 6 months of age: Ask a doctor

Inactive ingredients

Aqua (Water/Eau), Isoeicosane, Potassium Cetyl Phosphate, Cetearyl Alcohol, Cetyl Dimethicone, Dimethicone, Ethylhexyl Methoxycrylene, Glycerin, Hydroxyethyl Acrylate/Sodium Acryloyldimethyl Taurate Copolymer, Silica, Sorbitan Sesquioleate, Isohexadecane, Phenoxyethanol, Caprylyl Glycol, Ethylhexylglycerin, Polysorbate 60, Hexylene Glycol, Citric Acid. May Contain: CI 77891 (Titanium Dioxide), CI 77491, 77492, 77499 (Iron Oxides)

Other Information

• protect the product in this container from excessive
heat and direct sun

Purpose

Sunscreen

Packaging

Keep out of reach of children